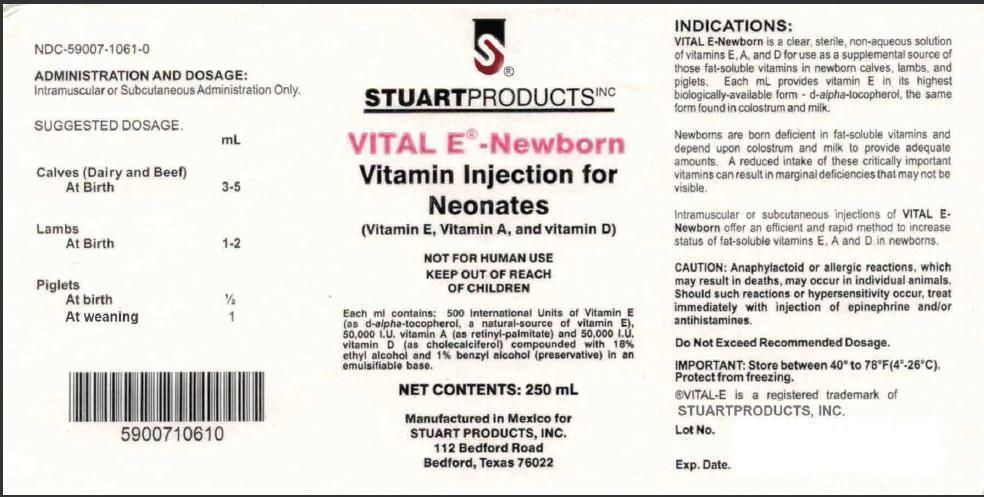 DRUG LABEL: Vital E
NDC: 59007-1061 | Form: INJECTION, EMULSION
Manufacturer: Stuart Products, Inc.
Category: animal | Type: OTC ANIMAL DRUG LABEL
Date: 20151008

ACTIVE INGREDIENTS: ALPHA-TOCOPHEROL, D- 500 [iU]/1 mL; VITAMIN A PALMITATE 50000 [iU]/1 mL; CHOLECALCIFEROL 50000 [iU]/1 mL
INACTIVE INGREDIENTS: ALCOHOL 180 1/1 mL; BENZYL ALCOHOL 10 1/1 mL

INDICATIONS:

VITAL E–Newborn is a clear, sterile, non-aqueous solution of vitamins E, A and D for use as a supplemental source of vitamin E, vitamin A and vitamin D in newborn calves, lambs and piglets. Each mL provides Vitamin E in its highest biologically-available form d-alpha tocopherol, the same form found in colostrum and milk.

Newborns are born deficient in fat-soluble vitamins and depend on colostrum and milk to provide adequate amounts. A reduced intake of these critically important vitamins can result in marginal deficiencies that may not be visible.

Intramuscular or subcutaneous injections of VITAL E-Newborn offer an efficient and rapid method to increase the status of vitamins E, A and D in newborns.

ADMINISTRATION AND DOSAGE:

Intramuscular or Subcutaneous Adminstration Only.

SUGGESTED DOSAGE:

Calves (Dairy and Beef)

At Birth 3-5 mL

Lambs

At Birth 1-2 mL

Piglets

At birth 1/2 mL

At weaning 1 mL

PRECAUTIONS

CAUTION: Anaphylactoid or allergic reactions, which may result in deaths, may occur in individual animals. Should such reactions or hypersensitivity occur, treat immediately with injection of epinephrine and/or antihistamines.

Do Not Exceed Recommended Dosage.

STORAGE AND HANDLING

IMPORTANT: Stored between 40° to 78° F (4°-26°C). Protect form freezing.

®VITAL-E is a registered trademark of

STUART PRODUCTS, INC.

Principal Display Panel - 250 mL Bottle

STUART PRODUCTS INC

VITAL E® - Newborn

Vitamin Injection for Neonates

(Vitamin E, Vitamin A, and vitamin D)

NOT FOR HUMAN USE

KEEP OUT OF REACH OF CHILDREN

Each ml contains: 500 international Units of Vitamin E (as d-alpha-tocopherol, a natural-source of vitamin E), 50,000 I.U. vitamin A (as retinyl-palmitate) and 50,000 I.U. vitamin D (as cholecalciferol) compounded with 18% ethyl alcohol and 1% benzyl alcohol (preservative) in an emulsifiable base.

NET CONTENTS: 250 mL

Manufactured in Mexico for

STUART PRODUCTS, INC.

112 Bedford Road

Bedford, Texas 76022